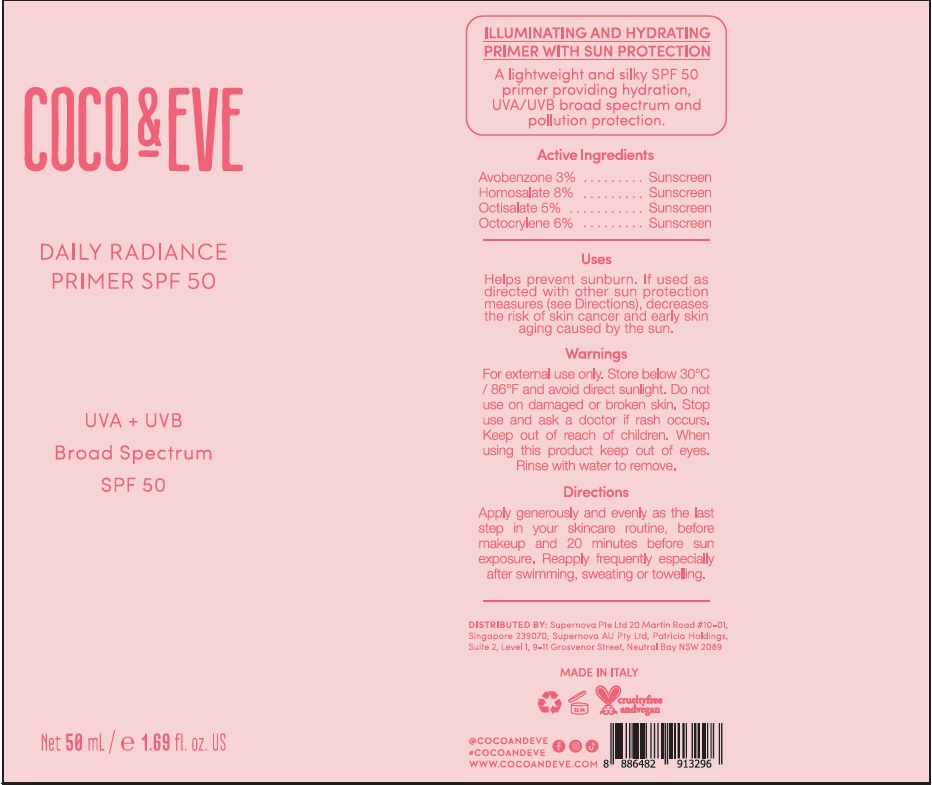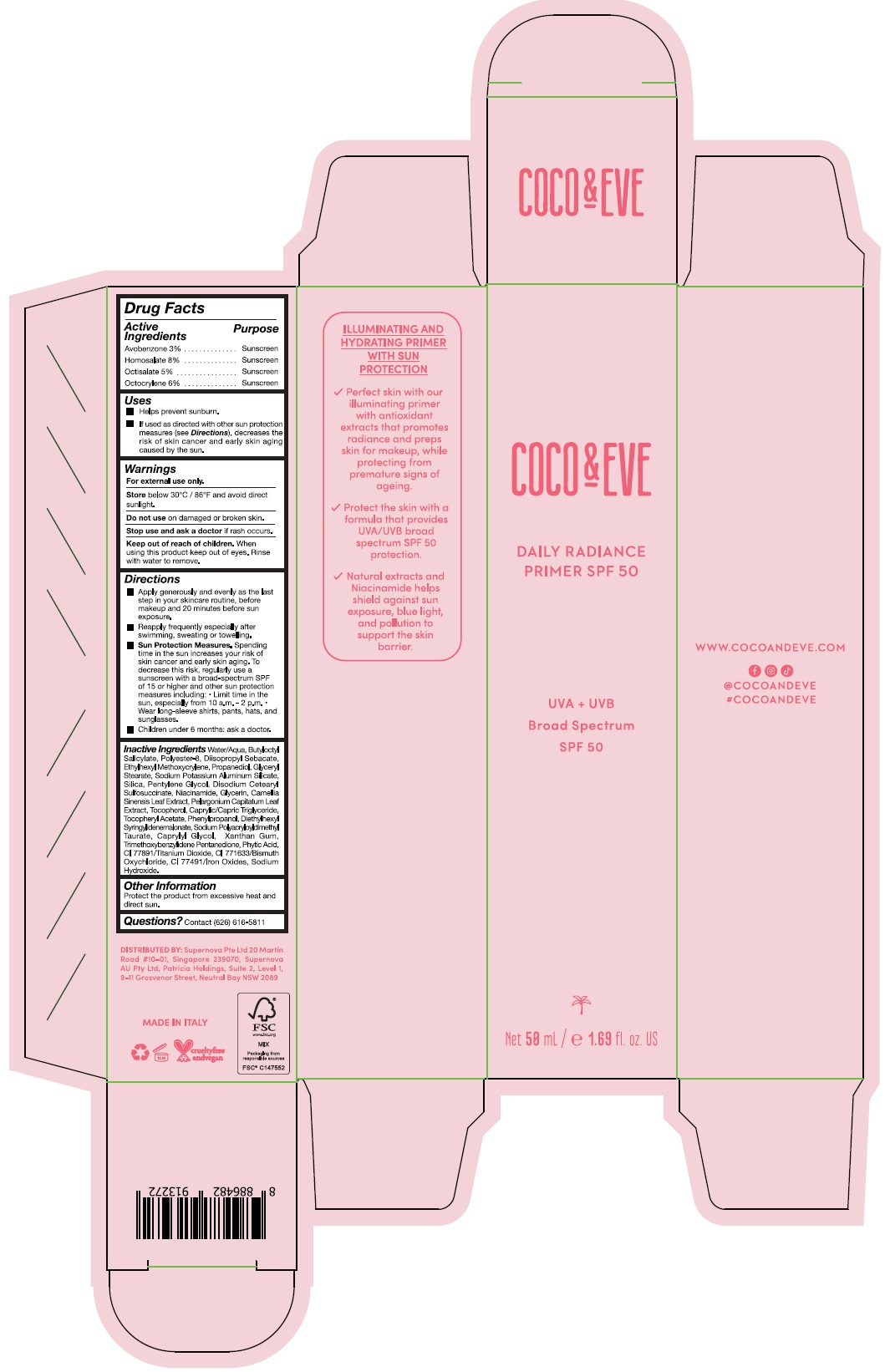 DRUG LABEL: COCO AND EVE DAILY RADIANCE PRIMER SPF 50
NDC: 82931-002 | Form: LOTION
Manufacturer: Supernova USA Inc.
Category: otc | Type: HUMAN OTC DRUG LABEL
Date: 20230331

ACTIVE INGREDIENTS: HOMOSALATE 8 g/100 mL; OCTOCRYLENE 6 g/100 mL; OCTISALATE 5 g/100 mL; AVOBENZONE 3 g/100 mL
INACTIVE INGREDIENTS: WATER; BUTYLOCTYL SALICYLATE; POLYESTER-8 (1400 MW, CYANODIPHENYLPROPENOYL CAPPED); DIISOPROPYL SEBACATE; ETHYLHEXYL METHOXYCRYLENE; PROPANEDIOL; GLYCERYL MONOSTEARATE; SODIUM POTASSIUM ALUMINUM SILICATE; SILICON DIOXIDE; PENTYLENE GLYCOL; DISODIUM STEARYL SULFOSUCCINATE; GLYCERIN; PHENYLPROPANOL; BISMUTH OXYCHLORIDE; NIACINAMIDE; DIETHYLHEXYL SYRINGYLIDENEMALONATE; SODIUM POLYACRYLOYLDIMETHYL TAURATE; TITANIUM DIOXIDE; CAPRYLYL GLYCOL; .ALPHA.-TOCOPHEROL ACETATE; XANTHAN GUM; TRIMETHOXYBENZYLIDENE PENTANEDIONE; FYTIC ACID; MEDIUM-CHAIN TRIGLYCERIDES; FERRIC OXIDE RED; PELARGONIUM CAPITATUM LEAF; GREEN TEA LEAF; TOCOPHEROL; SODIUM HYDROXIDE

COCO & EVE DAILY RADIANCE PRIMER SPF 50

Drug Facts

Active Ingredients
Avobenzone 3%
Homosalate 8%
Octisalate 5%
Octocrylene 6%

Purpose
Sunscreen
Sunscreen
Sunscreen
Sunscreen

Uses

- Helps prevent sunburn.
- If used as directed with other sun protection measures (see Directions), decreases the risk of skin cancer and early skin aging caused by the sun.

Warnings

For external use only.

Store below 30°C / 86°F and avoid direct sunlight.

Do not use on damaged or broken skin.

Stop use and ask a doctor if rash occurs.

Keep out of reach of children. When using this product keep out of eyes. Rinse with water to remove.

Directions

- Apply generously and evenly as the last step in your skincare routine, before makeup and 20 minutes before sun exposure.
- Reapply frequently especially after swimming, sweating or towelling.
- Sun Protection Measures. Spending time in the sun increases your risk of skin cancer and early skin aging. To decrease this risk, regularly use a sunscreen with a broad-spectrum SPF of 15 or higher and other sun protection measures including:
  - limit time in the sun, especially from 10 a.m. - 2 p.m.
  - Wear long-sleeve shirts, pants, hats, and sunglasses.
- Children under 6 months: ask a doctor.

INACTIVE INGREDIENT

Inactive Ingredients Water/Aqua, Butyloctyl Salicylate, Polyester-8, Diisopropyl Sebacate, Ethylhexyl Methoxycrylene, Propanediol, Glyceryl Stearate, Sodium Potassium Aluminum Silicate, Silica, Pentylene Glycol, Disodium Cetearyl Sulfosuccinate, Niacinamide, Glycerin, Camellia Sinensis Leaf Extract, Pelargonium Capitatum Leaf Extract, Tocopherol, Caprylic/Capric Triglyceride, Tocopheryl Acetate, Phenylpropanol, Diethylhexyl Syringylidenemalonate, Sodium Polyacryloyldimethyl Taurate, Caprylyl Glycol, Xanthan Gum, Trimethoxybenzylidene Pentanedione, Phytic Acid, Cl 77891/Titanium Dioxide, Cl 771633/Bismuth Oxychloride, Cl 77491/Iron Oxides, Sodium Hydroxide.

Other Information

Protect the product from excessive heat and direct sun.

Questions? Contact (626) 616-5811

PRINCIPAL DISPLAY PANEL

COCO & EVE

DAILY RADIANCE

PRIMER SPF 50

UVA + UVB

Broad Spectrum

SPF 50

Net 50 mL / e 1.69 fl. oz. US

COCO & EVE

DAILY RADIANCE

PRIMER SPF 50

UVA + UVB

Broad Spectrum

SPF 50

Net 50 mL / e 1.69 fl. oz. US